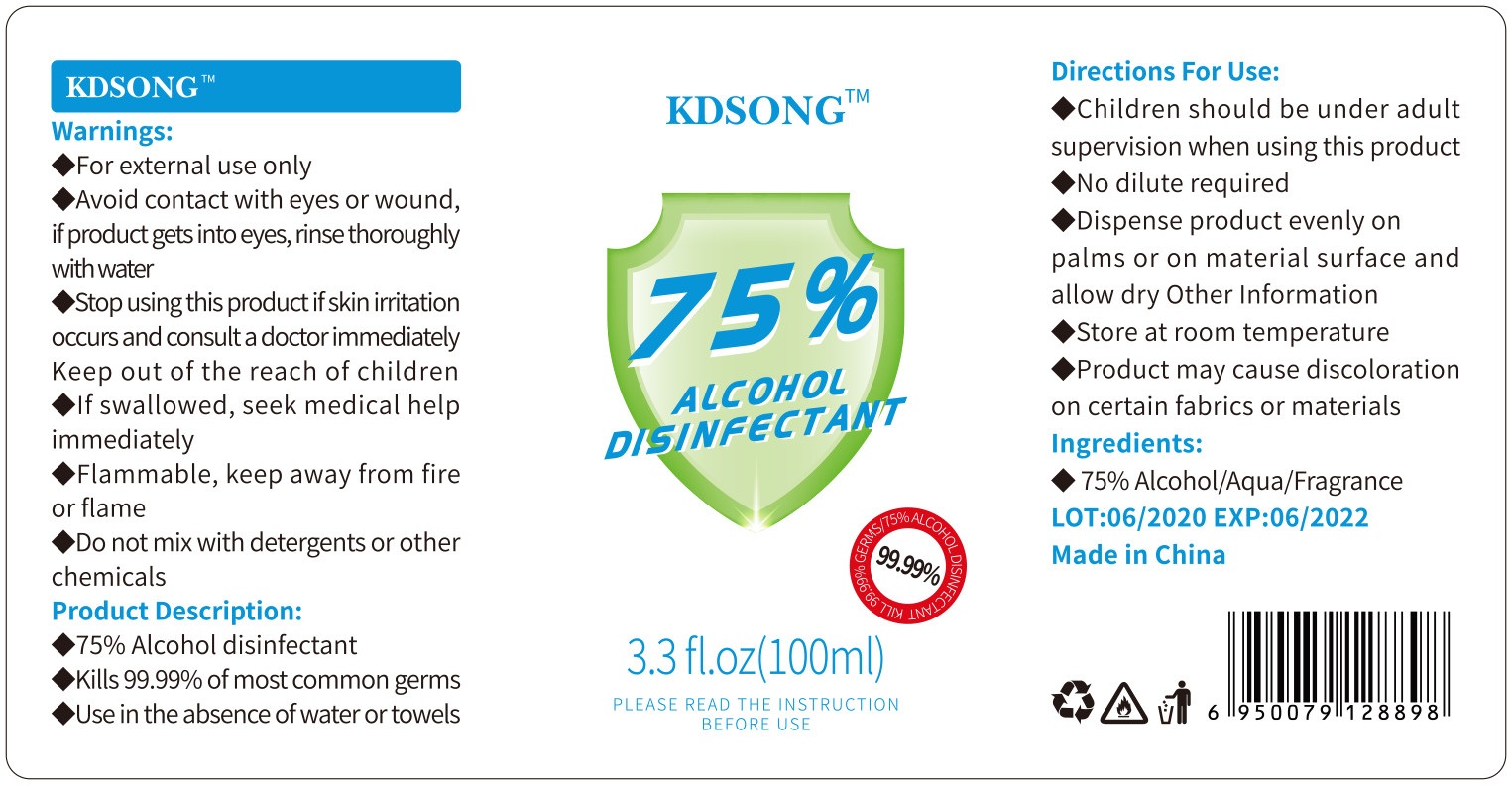 DRUG LABEL: 75% ALCOHOL DISINFECTANT
NDC: 54457-007 | Form: LIQUID
Manufacturer: GUANGZHOU ZUNAI DAILY COSMETICS CO., LTD
Category: otc | Type: HUMAN OTC DRUG LABEL
Date: 20200612

ACTIVE INGREDIENTS: ALCOHOL 75 mL/100 mL
INACTIVE INGREDIENTS: FRAGRANCE LAVENDER & CHIA F-153480; WATER

DOSAGE AND ADMINISTRATION

Store at room temperature

INACTIVE INGREDIENT

AQUA,FRAGRANCE

INDICATIONS AND USAGE

Place enough product on hands to cover all surfaces.

ACTIVE INGREDIENT

ALCOHOL

keep out of reach of children

PURPOSE

Disinfection
Sterilization

WARNINGS

◆Avoid contact with eyes or wound,if product gets into eyes, rinse thoroughlywith water
◆Stop using this product if skin iritation occurs and consult a doctor immediately Keep out of the reach of children
◆if swallowed, seek medical help immediately
◆Flammable, keep away from fire or flame